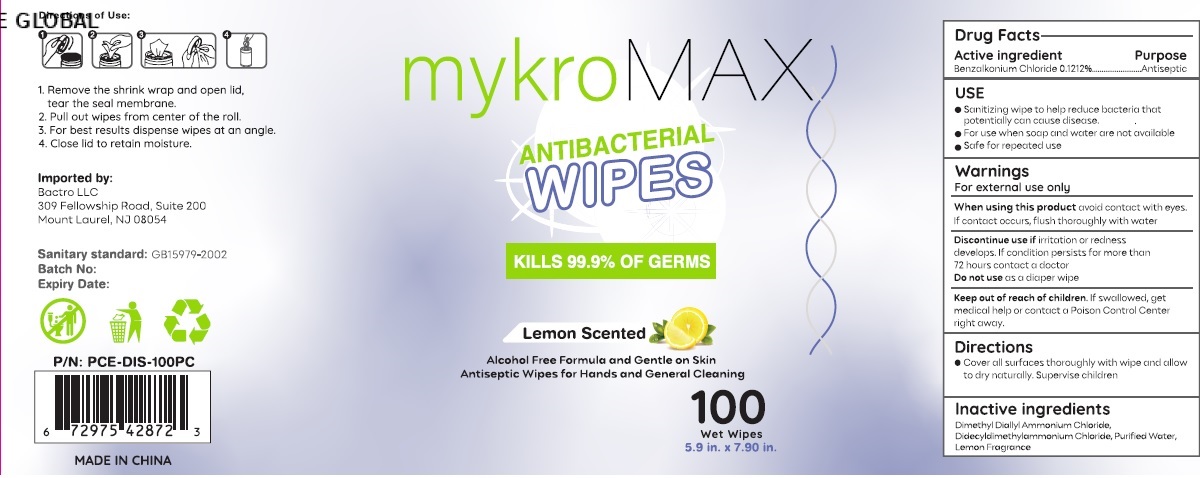 DRUG LABEL: Mykro Max Antibacterial wipes
NDC: 71734-330 | Form: SWAB
Manufacturer: JIANGMEN SHUIZIRUN SANITARY ARTICLES CO., LTD.
Category: otc | Type: HUMAN OTC DRUG LABEL
Date: 20201006

ACTIVE INGREDIENTS: benzalkonium chloride 0.1212 g/100 g
INACTIVE INGREDIENTS: water; DIMETHYL DIALLYL AMMONIUM CHLORIDE; DIDECYLDIMONIUM CHLORIDE

DRUG FACTS

Active Ingredient

Benzalkonium Chloride .......... 0.1212 %

Purpose

Antiseptic

Uses:

- Sanitizing wipe to help reduce bacteria that potentially can cause disease.
- For use when soap and water are not available.
- Safe for repeated use.

Warnings

For external use only.

When using this product avoid contact with eyes .If contact occurts ,flush thoroughly with water.

Discontinue use if irritation or redness develops . If conditon persists for more than 72 hours contact a doctor.

Do not use as a diaper wipe.

Keep out of reach of children.

if swallowed get medical help or contact a Poison Control Center right away.

Directions

Cover all surfaces thoroughly with wipe and allow to dry naturally .Supervise children under 6 years of age to avoid putting product in mouth.

Inactive Ingredients:

Dimethyl Diallyl Ammonium Chloride, Didecyldimethylammonium Chloride, Purified Water，Lemon Fragrance.